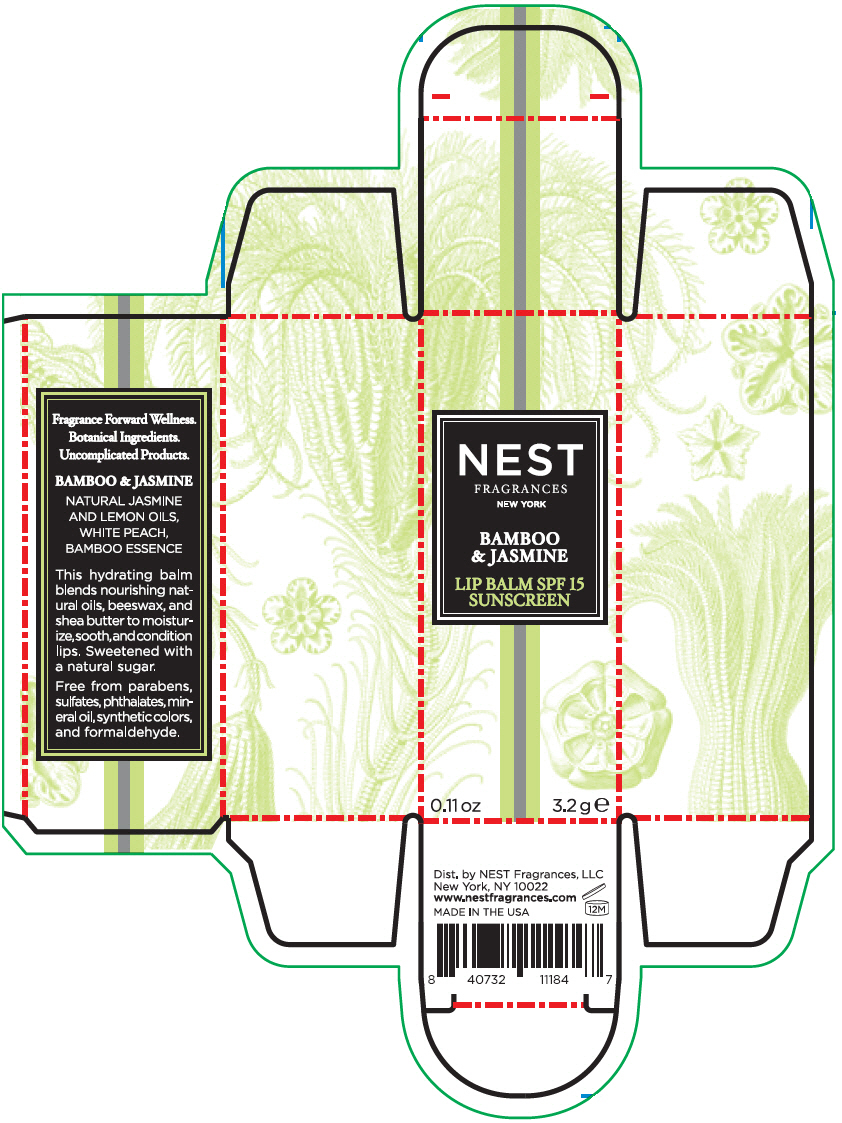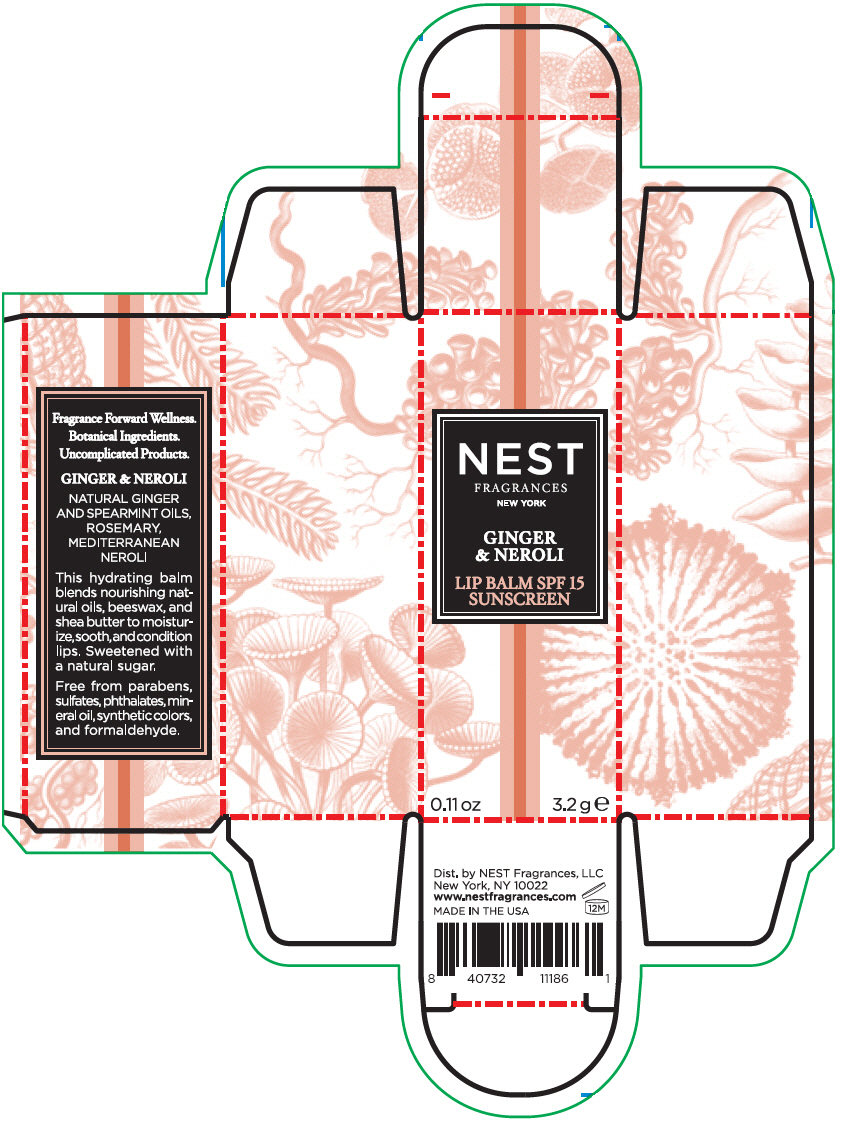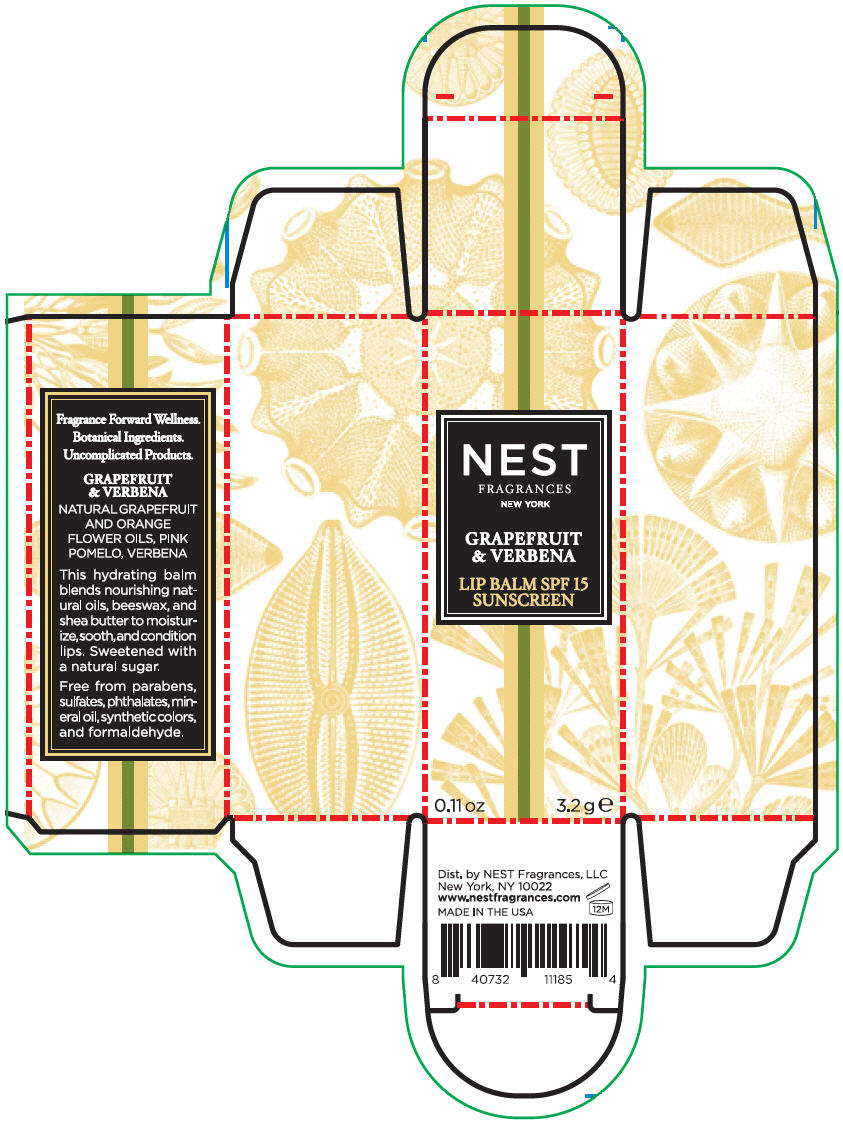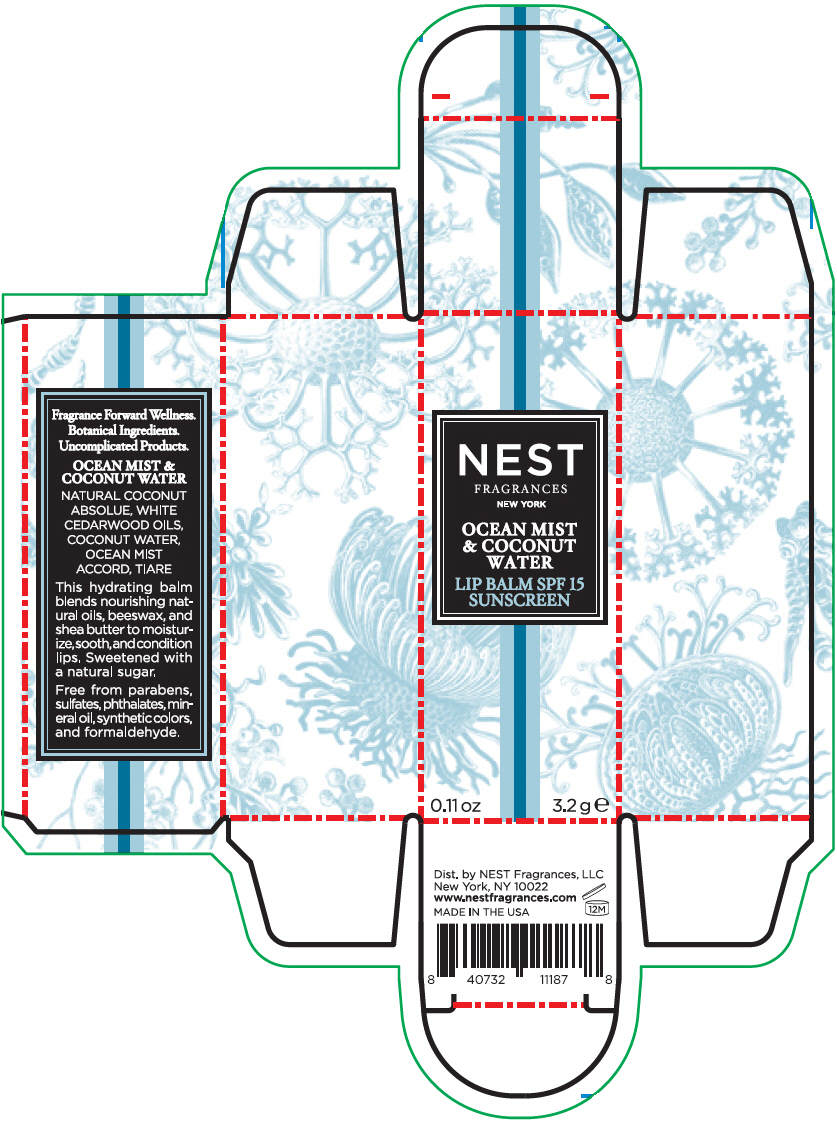 DRUG LABEL: NEST Fragrances 
NDC: 72556-001 | Form: STICK
Manufacturer: Nest Fragrances LLC
Category: otc | Type: HUMAN OTC DRUG LABEL
Date: 20181001

ACTIVE INGREDIENTS: Octinoxate 75 mg/1 g; Oxybenzone 20 mg/1 g
INACTIVE INGREDIENTS: WHITE WAX; MACADAMIA OIL; COCONUT OIL; GRAPE SEED OIL; JOJOBA OIL; CARNAUBA WAX; APRICOT KERNEL OIL; Erythritol; SUNFLOWER OIL

NEST Fragrances

Drug Facts

ACTIVE INGREDIENT

Active Ingredients: | Purpose
Octinoxate 7.5 % | Sunscreen
Oxybenzone 2.0 % | Sunscreen

Use

Helps prevent sunburn

Warnings

- Skin Cancer/Skin Aging Alert: Spending time in the sun increases your risk of skin cancer and early skin aging. This product has been shown only to help prevent sunburn, not skin cancer or early skin aging.

- For external use only

- Do not use on damaged or broken skin

- When using this product keep out of eyes. Rinse with water to remove.

STOP USE

- Stop using and ask a doctor if rash occurs

- Keep out of reach of children. If product is swallowed, get medical help or contact a Poison Control Center right away.

Directions

For sunscreen use

- Apply liberally 15 minutes before sun exposure.
- Use a water-resistant sunscreen if swimming or sweating.
- Re-apply at least every 2 hours.
- Children under 6 months: Ask a doctor.

Other information

- Protect this product in container from excessive heat and direct sun.

Inactive Ingredients

Beeswax (Cera Alba), Macadamia Ternifolia Seed Oil, Cocos Nucifera (Coconut) Oil, Vitis Vinifera (Grape) Seed Oil, Simmond- sia Chinensis (Jojoba) Seed Oil, Copernicia Cerifera (Carnauba) Wax, Prunus Armeniaca (Apricot) Kernel Oil, Shea Butter Ethyl Esters, Fragrance (Parfum), Erythritol, Flavor (Aroma), Tocopheryl Acetate, Rosma- rinus Officinalis (Rose- mary) Leaf Extract, Helianthus Annuus (Sunflower) Seed Oil.

Questions or comments?

Call toll-free 1-(888) 637-8510

Dist. by NEST Fragrances, LLC
New York, NY 10022

PRINCIPAL DISPLAY PANEL - 3.2 g Tube Carton - BAMBOO & JASMINE

NEST
FRAGRANCES

NEW YORK

BAMBOO
& JASMINE

LIP BALM SPF 15
SUNSCREEN

0.11 oz
3.2 g e

PRINCIPAL DISPLAY PANEL - 3.2 g Tube Carton - GINGER & NEROLI

NEST
FRAGRANCES

NEW YORK

GINGER
& NEROLI

LIP BALM SPF 15
SUNSCREEN

0.11 oz
3.2 g e

PRINCIPAL DISPLAY PANEL - 3.2 g Tube Carton - GRAPEFRUIT & VERBENA

NEST
FRAGRANCES

NEW YORK

GRAPEFRUIT
& VERBENA

LIP BALM SPF 15
SUNSCREEN

0.11 oz
3.2 g e

PRINCIPAL DISPLAY PANEL - 3.2 g Tube Carton - OCEAN MIST & COCONUT WATER

NEST
FRAGRANCES

NEW YORK

OCEAN MIST
& COCONUT
WATER

LIP BALM SPF 15
SUNSCREEN

0.11 oz
3.2 g e